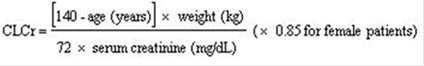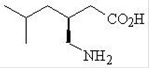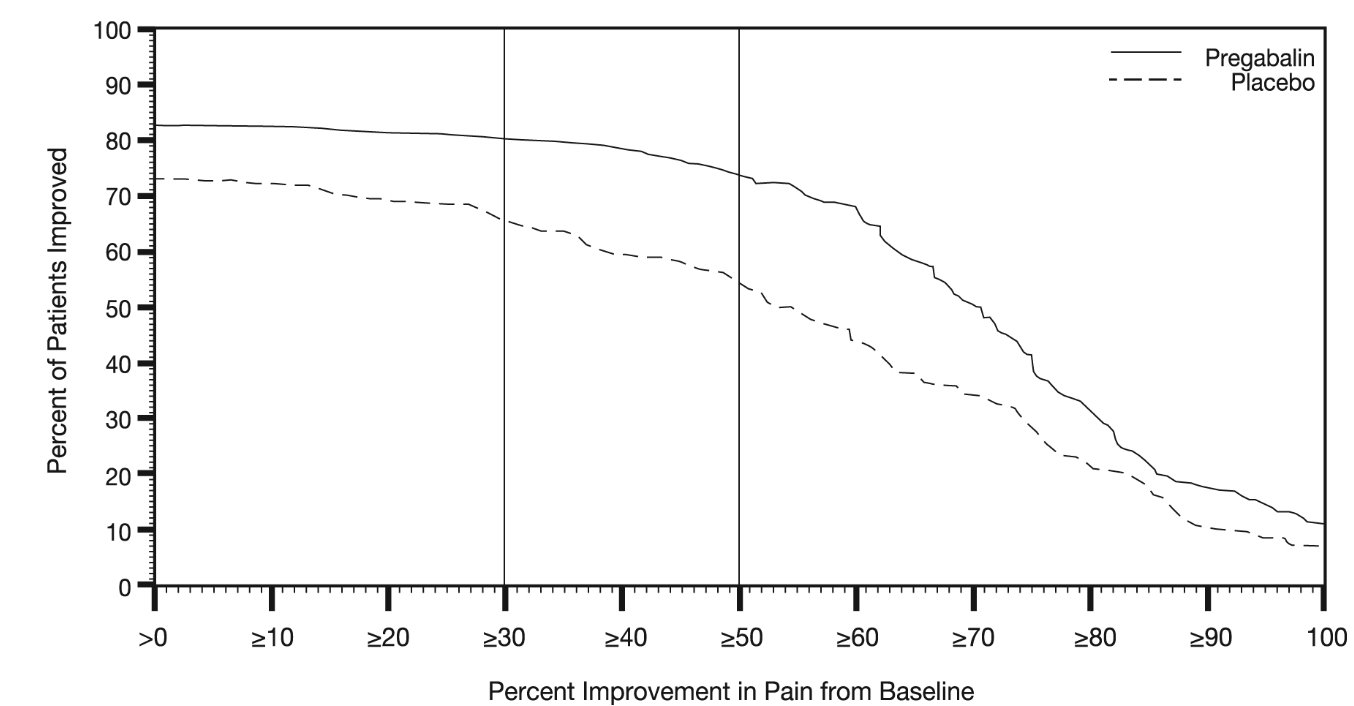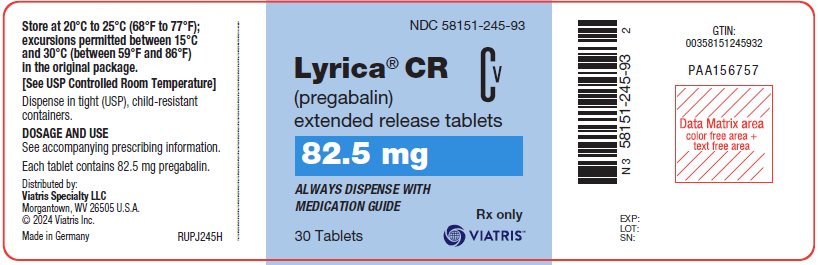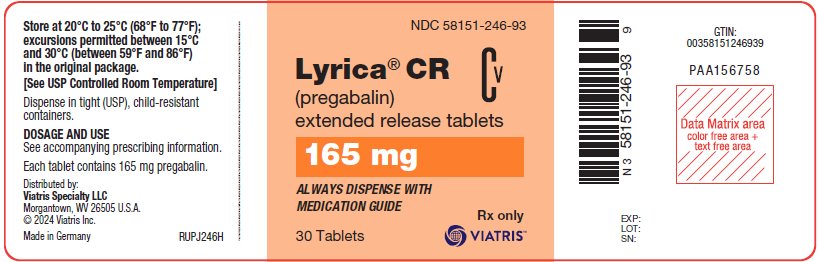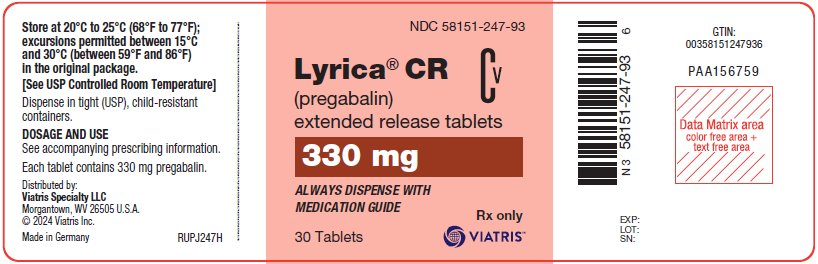 DRUG LABEL: Lyrica CR
NDC: 58151-245 | Form: TABLET, FILM COATED, EXTENDED RELEASE
Manufacturer: Viatris Specialty LLC
Category: prescription | Type: HUMAN PRESCRIPTION DRUG LABEL
Date: 20250409
DEA Schedule: CV

ACTIVE INGREDIENTS: PREGABALIN 82.5 mg/1 1
INACTIVE INGREDIENTS: CARBOMER HOMOPOLYMER, UNSPECIFIED TYPE; CROSPOVIDONE, UNSPECIFIED; KOLLIDON SR; MAGNESIUM STEARATE; POLYETHYLENE GLYCOL, UNSPECIFIED; POLYVINYL ALCOHOL, UNSPECIFIED; TALC; TITANIUM DIOXIDE

HIGHLIGHTS OF PRESCRIBING INFORMATION

These highlights do not include all the information needed to use LYRICA CR safely and effectively. See full prescribing information for LYRICA CR.
LYRICA® CR (pregabalin) extended-release tablets, for oral use, CV
Initial U.S. Approval: 2004

RECENT MAJOR CHANGES

Warnings and Precautions (5.3, 5.4) 04/2025

1 INDICATIONS AND USAGE

LYRICA CR is indicated for the management of:

- Neuropathic pain associated with diabetic peripheral neuropathy (DPN) (1)
- Postherpetic neuralgia (PHN) (1)

Efficacy of LYRICA CR has not been established for the management of fibromyalgia or as adjunctive therapy for adult patients with partial onset seizures.

2 DOSAGE AND ADMINISTRATION

- LYRICA CR should be administered once daily after an evening meal. It should be swallowed whole and should not be split, crushed, or chewed. (2.1)
- Dosing recommendations for LYRICA CR:

Indication | Dosing Regimen | Initial Dose | Maximum Dose
DPN Pain (2.2) | Single dose per day | 165 mg/day | 330 mg/day within 1 week.
PHN (2.3) | Single dose per day | 165 mg/day | 330 mg/day within 1 week. Maximum dose of 660 mg/day.

- Conversion from LYRICA Capsules or Oral Solution to LYRICA CR: See full prescribing information. (2.4)
- Dose modification recommended in patients with renal impairment. (2.5)

3 DOSAGE FORMS AND STRENGTHS

Extended-release tablets: 82.5 mg, 165 mg, and 330 mg. (3)

4 CONTRAINDICATIONS

Known hypersensitivity to pregabalin or any of its components. (4)

5 WARNINGS AND PRECAUTIONS

- Angioedema: Angioedema [e.g., swelling of the face, mouth (tongue, lips, and gums) and neck (throat and larynx)] can occur and may be associated with life-threatening respiratory compromise requiring emergency treatment. Discontinue LYRICA CR immediately in patients with these symptoms. (5.1)
- Hypersensitivity Reactions: Hypersensitivity reactions (e.g., hives, dyspnea, and wheezing) can occur. Discontinue LYRICA CR immediately in these patients. (5.2)
- Suicidal Behavior and Ideation: Antiepileptic drugs, including pregabalin, the active ingredient in LYRICA CR, increase the risk of suicidal thoughts or behavior. (5.3)
- Abrupt or rapid discontinuation may increase the risk for seizures. Withdrawal symptoms or suicidal behavior and ideation have been observed after discontinuation. Taper LYRICA CR gradually over a minimum of 1 week. (5.4)
- Respiratory Depression: May occur with LYRICA when used with concomitant CNS depressants or in the setting of underlying respiratory impairment. Monitor patients and adjust dosage as appropriate. (5.5)
- Dizziness and Somnolence: May cause dizziness and somnolence and impair patient’s ability to drive or operate machinery. (5.6)
- Peripheral Edema: May cause peripheral edema. Monitor patients for the development of edema when co-administering LYRICA CR and thiazolidinedione antidiabetic agents. (5.7)

6 ADVERSE REACTIONS

Most common adverse reactions reported in greater than or equal to 4% of patients treated with LYRICA CR are dizziness, somnolence, headache, fatigue, peripheral edema, nausea, blurred vision, dry mouth, and weight gain. (6.1)

To report SUSPECTED ADVERSE REACTIONS, contact Viatris at 1-877-446-3679 (1-877-4-INFO-RX) or FDA at 1-800-FDA-1088 or www.fda.gov/medwatch.

8 USE IN SPECIFIC POPULATIONS

- Lactation: Breastfeeding is not recommended. (8.2)

FULL PRESCRIBING INFORMATION

1 INDICATIONS AND USAGE

LYRICA CR is indicated for the management of:

- Neuropathic pain associated with diabetic peripheral neuropathy
- Postherpetic neuralgia

Efficacy of LYRICA CR has not been established for the management of fibromyalgia or as adjunctive therapy for adult patients with partial onset seizures.

2 DOSAGE AND ADMINISTRATION

2.1 Important Dosage and Administration Instructions

LYRICA CR should be administered once daily after an evening meal.

LYRICA CR should be swallowed whole and should not be split, crushed, or chewed.

When discontinuing LYRICA CR, taper gradually over a minimum of 1 week.

Instruct patients that if they miss taking their dose of LYRICA CR after an evening meal, then they should take their usual dose of LYRICA CR prior to bedtime following a snack. If they miss taking the dose of LYRICA CR prior to bedtime, then they should take their usual dose of LYRICA CR following a morning meal. If they miss taking the dose of LYRICA CR following the morning meal, then they should take their usual dose of LYRICA CR at the usual time that evening following an evening meal [see Patient Counseling Information (17)].

2.2 Neuropathic Pain Associated with Diabetic Peripheral Neuropathy

Begin dosing at 165 mg once daily and increase to 330 mg once daily within 1 week based on individual patient response and tolerability. The maximum recommended dose of LYRICA CR is 330 mg once daily.

Although LYRICA was studied at 600 mg/day, there was no evidence that this dose conferred additional significant benefit and this dose was less well tolerated. In view of the dose-dependent adverse reactions with LYRICA, treatment with doses above 330 mg/day is not recommended for LYRICA CR.

2.3 Postherpetic Neuralgia

Begin dosing at 165 mg once daily and increase to 330 mg once daily within 1 week based on individual patient response and tolerability.

Patients who do not experience sufficient pain relief following 2 to 4 weeks of treatment with 330 mg once daily and who are able to tolerate LYRICA CR, may be treated with up to 660 mg once daily. In view of the dose-dependent adverse reactions and the higher rate of treatment discontinuation due to adverse reactions, dosing above 330 mg/day should be reserved only for those patients who have on-going pain and are tolerating 330 mg daily. The maximum recommended dose of LYRICA CR is 660 mg once daily.

2.4 Conversion from LYRICA Capsules or Oral Solution to LYRICA CR

When switching from LYRICA to LYRICA CR on the day of the switch, instruct patients to take their morning dose of LYRICA as prescribed and initiate LYRICA CR therapy after an evening meal.

Table 1. Conversion from LYRICA Capsules or Oral Solution to LYRICA CR
LYRICA Total Daily Dose (dosed 2 or 3 times daily) | LYRICA CR Dose (dosed once a day)
75 mg/daily | 82.5 mg/day
150 mg/daily | 165 mg/day
225 mg/daily | 247.5 mg/day [247.5 mg = 3 × 82.5 mg tablets taken once a day.]
300 mg/daily | 330 mg/day
450 mg/daily | 495 mg/day [495 mg = 3 × 165 mg tablets taken once a day.]
600 mg/daily | 660 mg/day [660 mg = 2 × 330 mg tablets taken once a day.]

2.5 Patients with Renal Impairment

Use of LYRICA CR is not recommended for patients with creatinine clearance (CLcr) less than 30 mL/min or who are undergoing hemodialysis. Those patients should receive LYRICA.

In view of dose-dependent adverse reactions and because pregabalin is eliminated primarily by renal excretion, adjust the dose in patients with reduced renal function. Base the dose adjustment in patients with renal impairment on CLcr, as indicated in Table 2. To use the dosing tables, an estimate of the patient’s CLcr in mL/min is needed. CLcr in mL/min may be estimated from serum creatinine (mg/dL) determination using the Cockcroft and Gault equation:

Next, refer to the Dosage and Administration section to determine the recommended total daily dose based on indication, for a patient with normal renal function (CLcr greater than or equal to 60 mL/min). Then refer to Table 2 to determine the corresponding renal adjusted dose.

(For example: A patient initiating LYRICA CR therapy for postherpetic neuralgia with normal renal function [CLcr greater than or equal to 60 mL/min], receives a single daily dose of 165 mg/day pregabalin. Therefore, a renal impaired patient with a CLcr of 50 mL/min would receive a single daily dose of 82.5 mg.)

Table 2. LYRICA CR Dosage Adjustment Based on Renal Function
Creatinine Clearance (CLcr) (mL/min) | Total LYRICA CR Daily Dose (mg/day) |  |  |  | Dose Regimen
greater than or equal to 60 | 165 | 330 | 495 [495 mg = 3 × 165 mg tablets taken once a day.] | 660 [660 mg = 2 × 330 mg tablets taken once a day.] | Once a day
30-60 | 82.5 | 165 | 247.5 [247.5 mg = 3 × 82.5 mg tablets taken once a day.] | 330 | Once a day
less than 30/hemodialysis | Dose with LYRICA

3 DOSAGE FORMS AND STRENGTHS

Extended-release tablets: 82.5 mg, 165 mg, and 330 mg [see Description (11) and How Supplied/Storage and Handling (16)].

LYRICA CR Tablets
Tablet Strength (mg) | Tablet Description
82.5 mg | Light blue, film-coated, almond-shaped tablet debossed with “VLE” on one side and “PGN 82.5” on the other side
165 mg | Beige, film-coated, almond-shaped tablet debossed with “VLE” on one side and “PGN 165” on the other side
330 mg | Rose, film-coated, almond-shaped tablet debossed with “VLE” on one side and “PGN 330” on the other side

4 CONTRAINDICATIONS

LYRICA CR is contraindicated in patients with known hypersensitivity to pregabalin or any of its components. Angioedema and hypersensitivity reactions have occurred in patients receiving pregabalin therapy [see Warnings and Precautions (5.1, 5.2), Adverse Reactions (6)].

5 WARNINGS AND PRECAUTIONS

5.1 Angioedema

There have been postmarketing reports of angioedema in patients during initial and chronic treatment with LYRICA. Specific symptoms included swelling of the face, mouth (tongue, lips, and gums), and neck (throat and larynx). There were reports of life-threatening angioedema with respiratory compromise requiring emergency treatment. Discontinue LYRICA CR immediately in patients with these symptoms.

Exercise caution when prescribing LYRICA CR to patients who have had a previous episode of angioedema. In addition, patients who are taking other drugs associated with angioedema (e.g., angiotensin converting enzyme inhibitors [ACE-inhibitors]) may be at increased risk of developing angioedema.

5.2 Hypersensitivity Reactions

There have been postmarketing reports of hypersensitivity reactions in patients shortly after initiation of treatment with LYRICA. Adverse reactions included skin redness, blisters, hives, rash, dyspnea, and wheezing. Discontinue LYRICA CR immediately in patients with these symptoms.

5.3 Suicidal Behavior and Ideation

Antiepileptic drugs (AEDs), including pregabalin, the active ingredient in LYRICA CR, increase the risk of suicidal thoughts or behavior in patients taking these drugs for any indication. Suicidal behavior and ideation have also been reported in patients after discontinuation of pregabalin [see Warnings and Precautions (5.4)]. Monitor patients treated with any AED for any indication for the emergence or worsening of depression, suicidal thoughts or behavior, and/or any unusual changes in mood or behavior.

Pooled analyses of 199 placebo-controlled clinical trials (mono- and adjunctive therapy) of 11 different AEDs showed that patients randomized to one of the AEDs had approximately twice the risk (adjusted Relative Risk 1.8, 95% CI:1.2, 2.7) of suicidal thinking or behavior compared to patients randomized to placebo. In these trials, which had a median treatment duration of 12 weeks, the estimated incidence rate of suicidal behavior or ideation among 27,863 AED-treated patients was 0.43%, compared to 0.24% among 16,029 placebo-treated patients, representing an increase of approximately one case of suicidal thinking or behavior for every 530 patients treated. There were four suicides in drug-treated patients in the trials and none in placebo-treated patients, but the number is too small to allow any conclusion about drug effect on suicide.

The increased risk of suicidal thoughts or behavior with AEDs was observed as early as one week after starting drug treatment with AEDs and persisted for the duration of treatment assessed. Because most trials included in the analysis did not extend beyond 24 weeks, the risk of suicidal thoughts or behavior beyond 24 weeks could not be assessed.

The risk of suicidal thoughts or behavior was generally consistent among drugs in the data analyzed. The finding of increased risk with AEDs of varying mechanisms of action and across a range of indications suggests that the risk applies to all AEDs used for any indication. The risk did not vary substantially by age (5-100 years) in the clinical trials analyzed.

Table 3 shows absolute and relative risk by indication for all evaluated AEDs.

Table 3. Risk by Indication for Antiepileptic Drugs in the Pooled Analysis
Indication | Placebo Patients With Events per 1000 Patients | Drug Patients With Events per 1000 Patients | Relative Risk: Incidence of Events in Drug Patients/Incidence in Placebo Patients | Risk Difference: Additional Drug Patients With Events per 1000 Patients
Epilepsy | 1.0 | 3.4 | 3.5 | 2.4
Psychiatric | 5.7 | 8.5 | 1.5 | 2.9
Other | 1.0 | 1.8 | 1.9 | 0.9
Total | 2.4 | 4.3 | 1.8 | 1.9

The relative risk for suicidal thoughts or behavior was higher in clinical trials for epilepsy than in clinical trials for psychiatric or other conditions, but the absolute risk differences were similar for the epilepsy and psychiatric indications.

Anyone considering prescribing LYRICA CR must balance the risk of suicidal thoughts or behavior with the risk of untreated illness. Many other illnesses for which AEDs are prescribed are themselves associated with morbidity and mortality and an increased risk of suicidal thoughts and behavior. Should suicidal thoughts and behavior emerge during treatment, the prescriber needs to consider whether the emergence of these symptoms in any given patient may be related to the illness being treated.

Inform patients, their caregivers, and families that LYRICA CR can increase the risk of suicidal thoughts and behavior and advise them of the need to be alert for the emergence or worsening of the signs and symptoms of depression, any unusual changes in mood or behavior, or the emergence of suicidal thoughts, behavior, or thoughts about self-harm. Report behaviors of concern immediately to healthcare providers.

5.4 Increased Risk of Adverse Reactions with Abrupt or Rapid Discontinuation

Following abrupt or rapid discontinuation of LYRICA CR, some patients reported symptoms including, insomnia, nausea, headache, anxiety, and diarrhea [see Adverse Reactions (6.2), Drug Abuse and Dependence (9.3)]. Suicidal behavior and ideation have also been reported in patients after discontinuation of pregabalin [see Warnings and Precautions (5.3)]. Increased seizure frequency may occur in patients with seizure disorders taking LYRICA CR for pain if LYRICA CR is rapidly discontinued. Taper LYRICA CR gradually over a minimum of 1 week rather than discontinuing the drug abruptly. The efficacy of LYRICA CR as adjunctive therapy for adult patients with partial onset seizures has not been established.

5.5 Respiratory Depression

There is evidence from case reports, human studies, and animal studies associating pregabalin with serious, life-threatening, or fatal respiratory depression when co-administered with central nervous system (CNS) depressants, including opioids, or in the setting of underlying respiratory impairment. When the decision is made to co-prescribe LYRICA CR with another CNS depressant, particularly an opioid, or to prescribe LYRICA CR to patients with underlying respiratory impairment, monitor patients for symptoms of respiratory depression and sedation, and consider initiating LYRICA CR at a low dose. The management of respiratory depression may include close observation, supportive measures, and reduction or withdrawal of CNS depressants (including LYRICA CR).

There is more limited evidence from case reports, animal studies, and human studies associating pregabalin with serious respiratory depression, without co-administered CNS depressants or without underlying respiratory impairment.

5.6 Dizziness and Somnolence

LYRICA CR may cause dizziness and somnolence. Inform patients that LYRICA CR-related dizziness and somnolence may impair their ability to perform tasks such as driving or operating machinery. Concomitant use of LYRICA CR with other central nervous system (CNS) depressants may exacerbate these effects [see Drug Interactions (7)].

In the LYRICA CR controlled trials for pain indications, dizziness was experienced by 24% of LYRICA CR‑treated patients during the single‑blind phase; somnolence was experienced by 15.8% of LYRICA CR-treated patients. Dizziness and somnolence generally began shortly after the initiation of LYRICA CR therapy and occurred more frequently at higher doses. Dizziness and somnolence were the adverse reactions most frequently leading to withdrawal (2.4%, 1.2% each) during the single‑blind phase of the controlled studies. In LYRICA-treated patients reporting these adverse reactions in short‑term, controlled studies, dizziness persisted until the last dose in 30% and somnolence persisted until the last dose in 42% of patients.

5.7 Peripheral Edema

LYRICA CR treatment may cause peripheral edema. In short-term trials of patients without clinically significant heart or peripheral vascular disease, there was no apparent association between peripheral edema and cardiovascular complications such as hypertension or congestive heart failure. Peripheral edema was not associated with laboratory changes suggestive of deterioration in renal or hepatic function.

In controlled clinical trials for pain indications, the incidence of peripheral edema for patients receiving LYRICA CR in the single-blind phase was 5.3% of patients. In controlled clinical trials for pain indications, 0.8% of LYRICA CR patients withdrew due to peripheral edema during the single-blind phase.

Higher frequencies of weight gain and peripheral edema were observed in patients taking both LYRICA and a thiazolidinedione antidiabetic agent compared to patients taking either drug alone. The majority of patients using thiazolidinedione antidiabetic agents in the overall safety database were participants in studies of pain associated with diabetic peripheral neuropathy. In this population, peripheral edema was reported in 3% (2/60) of patients who were using thiazolidinedione antidiabetic agents only, 8% (69/859) of patients who were treated with LYRICA only, and 19% (23/120) of patients who were on both LYRICA and thiazolidinedione antidiabetic agents. Similarly, weight gain was reported in 0% (0/60) of patients on thiazolidinediones only; 4% (35/859) of patients on LYRICA only; and 7.5% (9/120) of patients on both drugs.

As the thiazolidinedione class of antidiabetic drugs can cause weight gain and/or fluid retention, possibly exacerbating or leading to heart failure, monitor patients for the development of edema when co-administering LYRICA CR and these agents.

Because there are limited data on congestive heart failure patients with New York Heart Association (NYHA) Class III or IV cardiac status, monitor these patients for possible exacerbation of congestive heart failure symptoms when using LYRICA CR.

5.8 Weight Gain

LYRICA CR treatment may cause weight gain. In LYRICA CR controlled trials for pain indications, weight gain was experienced by 4% of LYRICA CR-treated patients during the single-blind phase. Adverse events of weight gain were observed in 3.7% of LYRICA CR-treated patients and 1% of placebo-treated patients during the double-blind phase.

In LYRICA controlled clinical trials of up to 14 weeks a gain of 7% or more over baseline weight was observed in 9% of LYRICA-treated patients and 2% of placebo-treated patients. Few patients treated with LYRICA (0.3%) withdrew from controlled trials due to weight gain. In studies with LYRICA, associated weight gain was related to pregabalin dose and duration of exposure but did not appear to be associated with baseline BMI, gender, or age. Weight gain was not limited to patients with edema [see Warnings and Precautions (5.7)].

Although weight gain was not associated with clinically important changes in blood pressure in short-term controlled studies with LYRICA, the long-term cardiovascular effects of pregabalin-associated weight gain are unknown.

Among diabetic patients, LYRICA-treated patients gained an average of 1.6 kg (range: -16 to 16 kg), compared to an average 0.3 kg (range: -10 to 9 kg) weight gain in placebo patients. In a cohort of 333 diabetic patients who received LYRICA for at least 2 years, the average weight gain was 5.2 kg.

While the effects of pregabalin-associated weight gain on glycemic control have not been systematically assessed, in controlled and longer-term open-label clinical trials with diabetic patients, LYRICA treatment did not appear to be associated with loss of glycemic control (as measured by HbA1C).

5.9 Tumorigenic Potential

In standard preclinical in vivo lifetime carcinogenicity studies of pregabalin, an unexpectedly high incidence of hemangiosarcoma was identified in 2 different strains of mice [see Nonclinical Toxicology (13.1)]. The clinical significance of this finding is unknown. Clinical experience during premarketing development of LYRICA provides no direct means to assess its potential for inducing tumors in humans.

In clinical studies across various patient populations, comprising 6396 patient-years of exposure in patients greater than 12 years of age, new or worsening preexisting tumors were reported in 57 patients. Without knowledge of the background incidence and recurrence in similar populations not treated with pregabalin, it is impossible to know whether the incidence seen in these cohorts is or is not affected by treatment.

5.10 Ophthalmological Effects

In controlled studies for pain indications, 4.8% of patients treated with LYRICA CR in the single-blind phase reported blurred vision, which resolved in a majority of cases with continued dosing. Less than 1% of patients discontinued LYRICA CR treatment due to vision-related events (primarily blurred vision). Additionally, 0.7% of LYRICA CR-treated patients as compared to no placebo-treated patients experienced blurred vision in the double-blind phase.

Prospectively planned ophthalmologic testing during the premarketing development of pregabalin, including visual acuity testing, formal visual field testing and dilated funduscopic examination, was performed in over 3600 patients. In these patients, visual acuity was reduced in 7% of LYRICA-treated patients and 5% of placebo-treated patients. Visual field changes were detected in 13% of LYRICA-treated and 12% of placebo-treated patients. Funduscopic changes were observed in 2% of LYRICA-treated and 2% of placebo-treated patients.

Although the clinical significance of the ophthalmologic findings is unknown, inform patients to notify their physician if changes in vision occur. If visual disturbance persists, consider further assessment. Consider more frequent assessment for patients who are already routinely monitored for ocular conditions.

5.11 Creatine Kinase Elevations

LYRICA treatment was associated with creatine kinase elevations. Mean changes in creatine kinase from baseline to the maximum value were 60 U/L for LYRICA‑treated patients and 28 U/L for the placebo patients. In all controlled trials across multiple patient populations, 1.5% of patients on LYRICA and 0.7% of placebo patients had a value of creatine kinase at least 3 times the upper limit of normal. Three LYRICA‑treated subjects had events reported as rhabdomyolysis in premarketing clinical trials. The relationship between these myopathy events and LYRICA is not completely understood because the cases had documented factors that may have caused or contributed to these events. Instruct patients to promptly report unexplained muscle pain, tenderness, or weakness, particularly if these muscle symptoms are accompanied by malaise or fever. Discontinue treatment with LYRICA CR if myopathy is diagnosed or suspected or if markedly elevated creatine kinase levels occur.

5.12 Decreased Platelet Count

Both LYRICA CR and LYRICA treatment were associated with a decrease in platelet count. In the double‑blind phase of controlled studies for pain indication, LYRICA CR‑treated patients experienced a median change from baseline in platelet count of 11 × 10^3/mm^3 (for the PHN population) and 14 × 10^3/mm^3 (for the FM population) as compared to 1 × 10^3/mm^3 in placebo‑treated patients (for both populations). LYRICA‑treated patients experienced a mean maximal decrease in platelet count of 20 × 10^3/µL, compared to 11 × 10^3/µL in placebo patients. In the overall database of controlled trials, 2% of placebo patients and 3% of LYRICA patients experienced a potentially clinically significant decrease in platelets, defined as 20% below baseline value and less than 150 × 10^3/µL. A single LYRICA‑treated subject developed severe thrombocytopenia with a platelet count less than 20 × 10^3/µL. In randomized controlled trials, LYRICA or LYRICA CR were not associated with an increase in bleeding‑related adverse reactions.

5.13 PR Interval Prolongation

LYRICA treatment was associated with PR interval prolongation. In analyses of clinical trial ECG data, the mean PR interval increase was 3-6 msec at pregabalin doses greater than or equal to 300 mg/day. This mean change difference was not associated with an increased risk of PR increase greater than or equal to 25% from baseline, an increased percentage of subjects with on‑treatment PR greater than 200 msec, or an increased risk of adverse reactions of second or third degree AV block.

Subgroup analyses did not identify an increased risk of PR prolongation in patients with baseline PR prolongation or in patients taking other PR prolonging medications. However, these analyses cannot be considered definitive because of the limited number of patients in these categories.

6 ADVERSE REACTIONS

The following adverse reactions are described elsewhere in the labeling:

- Angioedema [see Warnings and Precautions (5.1)]
- Hypersensitivity Reactions [see Warnings and Precautions (5.2)]
- Suicidal Behavior and Ideation [see Warnings and Precautions (5.3)]
- Increased Risk of Adverse Reactions with Abrupt or Rapid Discontinuation [see Warnings and Precautions (5.4)]
- Respiratory Depression [see Warnings and Precautions (5.5)]
- Dizziness and Somnolence [see Warnings and Precautions (5.6)]
- Peripheral Edema [see Warnings and Precautions (5.7)]
- Weight Gain [see Warnings and Precautions (5.8)]
- Ophthalmological Effects [see Warnings and Precautions (5.10)]
- Creatine Kinase Elevations [see Warnings and Precautions (5.11)]
- Decreased Platelet Count [see Warnings and Precautions (5.12)]

6.1 Clinical Trials Experience

Because clinical trials are conducted under widely varying conditions, adverse reaction rates observed in the clinical trials of a drug cannot be directly compared to rates in the clinical trials of another drug and may not reflect the rates observed in practice.

Two randomized placebo-controlled clinical trials were conducted in patients with postherpetic neuralgia and fibromyalgia in which a total of 1242 patients received LYRICA CR. Both studies were randomized withdrawal design where a 6-week single-blind, dose optimization phase was followed by a 13-week double-blind phase. The most common adverse events leading to discontinuation from the single-blind phase of the study occurring in greater than or equal to 0.3% of patients were dizziness, somnolence, peripheral edema, fatigue, blurred vision, and increased weight. Sixty-four percent of patients experienced adverse events during the single-blind phase, with the most common adverse events occurring in greater than or equal to 4% of patients being dizziness, somnolence, headache, fatigue, peripheral edema, nausea, blurred vision, dry mouth, and weight gain.

Controlled Study in Postherpetic Neuralgia

Adverse Reactions Leading to Discontinuation

In a clinical trial in patients with postherpetic neuralgia, 8.9% of patients treated with LYRICA CR discontinued prematurely during the single-blind phase due to adverse reactions. The most common reasons for discontinuation due to adverse reactions were dizziness (2.1%), somnolence (0.87%), and peripheral edema (0.50%).

Most Common Adverse Reactions

Table 4 lists all adverse reactions, regardless of causality, occurring in greater than or equal to 1% of patients with postherpetic neuralgia who received LYRICA CR, regardless of the phase of the study.

Table 4. Incidence of Adverse Reactions Reported in Greater Than or Equal to 1% of Subjects in Any Phase of the LYRICA CR Study in Patients with Postherpetic Neuralgia*
System Organ Class Preferred Term | Single-Blind Phase | Double-Blind Phase
System Organ Class Preferred Term | LYRICA CR [N=801] n (%) | LYRICA CR [N=208] n (%) | Placebo [N=205] n (%)
Ear and labyrinth disorders
Vertigo | 31 (3.9) | 2 (1.0) | 1 (0.5)
Eye disorders
Vision blurred | 30 (3.7) | 1 (0.5) | 0
Diplopia | 8 (1.0) | 1 (0.5) | 0
Gastrointestinal disorders
Dry mouth | 30 (3.7) | 1 (0.5) | 0
Nausea | 24 (3.0) | 7 (3.4) | 0
Constipation | 22 (2.7) | 0 | 0
Diarrhea | 11 (1.4) | 2 (1.0) | 1 (0.5)
Vomiting | 9 (1.1) | 3 (1.4) | 1 (0.5)
General disorders and administration site conditions
Edema peripheral | 39 (4.9) | 8 (3.8) | 1 (0.5)
Fatigue | 31 (3.9) | 3 (1.4) | 2 (1.0)
Edema | 3 (0.4) | 3 (1.4) | 0
Infections and infestations
Nasopharyngitis | 12 (1.5) | 3 (1.4) | 0
Urinary tract infection | 11 (1.4) | 3 (1.4) | 1 (0.5)
Bronchitis | 4 (0.5) | 3 (1.4) | 2 (1.0)
Respiratory tract infection viral | 3 (0.4) | 3 (1.4) | 1 (0.5)
Sinusitis | 3 (0.4) | 2 (1.0) | 0
Gastroenteritis viral | 2 (0.2) | 2 (1.0) | 0
Investigations
Weight increased | 20 (2.5) | 8 (3.8) | 2 (1.0)
Alanine aminotransferase increased | 2 (0.2) | 3 (1.4) | 0
Aspartate aminotransferase increased | 2 (0.2) | 2 (1.0) | 0
Musculoskeletal and connective tissue disorders
Arthralgia | 6 (0.7) | 2 (1.0) | 1 (0.5)
Joint swelling | 0 | 4 (1.9) | 0
Nervous system disorders
Dizziness | 137 (17.1) | 7 (3.4) | 1 (0.5)
Somnolence | 91 (11.4) | 1 (0.5) | 0
Headache | 31 (3.9) | 4 (1.9) | 1 (0.5)
Balance disorder | 21 (2.6) | 1 (0.5) | 0
Reproductive system and breast disorders
Erectile dysfunction | 2 (0.6) | 1 (1.4) | 0
Respiratory, thoracic, and mediastinal disorders
Cough | 2 (0.2) | 2 (1.0) | 1 (0.5)
Skin and subcutaneous tissue disorders
Dermatitis contact | 0 | 2 (1.0) | 0
* Table is limited to adverse reactions that occurred with higher incidence in LYRICA CR-treated patients than in placebo-treated patients for the DB Phase of the study.

Other Adverse Reactions Observed During Clinical Studies with LYRICA and LYRICA CR

In addition to the adverse reactions reported during the controlled studies with LYRICA CR in postherpetic neuralgia, the following adverse reactions have been reported in patients treated with LYRICA and LYRICA CR during all clinical studies. This listing does not include those adverse reactions already listed above. The adverse reactions are categorized by system organ class and listed in order of decreasing frequency according to the following definitions: frequent adverse reactions are those occurring on 1 or more occasions in at least 1/100 patients; infrequent adverse reactions are those occurring in 1/100 to 1/1000 patients; rare reactions are those occurring in fewer than 1/1000 patients. Adverse reactions of major clinical importance are described in the Warnings and Precautions section (5).

Cardiac Disorders – Infrequent: Palpitations, Deep thrombophlebitis, Heart failure, Hypotension, Postural hypotension, Retinal vascular disorder, Syncope; Rare: Cardiac failure, Tachycardia

Eye Disorders – Infrequent: Periorbital edema

Gastrointestinal Disorders – Frequent: Increased appetite; Infrequent: Abdominal distension, Abdominal pain, Dysphagia, Pancreatitis, Tongue edema

General Disorders – Frequent: Fever; Infrequent: Chest pain, Face edema; Rare: Facial pain, Mucosal dryness

Hemic and Lymphatic System Disorders – Frequent: Ecchymosis; Infrequent: Anemia, Eosinophilia, Hypochromic anemia, Leukocytosis, Leukopenia, Lymphadenopathy, Thrombocytopenia; Rare: Myelofibrosis, Polycythemia, Prothrombin decreased, Purpura, Thrombocythemia

Infections and Infestations – Infrequent: Otitis media, Pneumonia

Investigations – Rare: Glucose urine present, Lipase increased, Neutrophil count increased, Proteinuria

Metabolic and Nutritional Disorders – Rare: Glucose Tolerance Decreased, Urate Crystalluria

Musculoskeletal and Connective Tissue Disorders – Frequent: Leg cramps, Myalgia, Myasthenia; Infrequent: Joint stiffness; Rare: Coccydynia, Myokymia

Nervous System Disorders – Frequent: Anxiety, Depersonalization, Hypertonia, Hypoesthesia, Libido decreased, Nystagmus, Paresthesia, Sedation, Stupor, Twitching; Infrequent: Coordination abnormal, Abnormal dreams, Agitation, Amnesia, Apathy, Aphasia, Circumoral paresthesia, Cognitive disorder, Dysarthria, Dysgeusia, Hallucinations, Hostility, Hyperalgesia, Hyperesthesia, Hyperkinesia, Hypokinesia, Hypotonia, Libido increased, Myoclonus, Neuralgia, Sciatica, Sleep phase rhythm disturbance; Rare: Addiction, Altered state of consciousness, Bradykinesia, Cerebellar syndrome, Cogwheel rigidity, Coma, Delirium, Delusions, Depressed level of consciousness, Dysautonomia, Dyskinesia, Dystonia, Encephalopathy, Extrapyramidal syndrome, Psychomotor hyperactivity, Psychomotor skills impaired

Psychiatric Disorders – Infrequent: Irritability

Respiratory System Disorders – Rare: Lung edema

Skin Disorders – Frequent: Pruritus; Rare: Stevens-Johnson syndrome

Special Senses – Frequent: Conjunctivitis, Tinnitus

Urogenital System Disorders – Frequent: Anorgasmia, Impotence, Urinary frequency, Urinary incontinence; Infrequent: Abnormal ejaculation, Albuminuria, Dysuria, Hematuria, Kidney calculus, Leukorrhea, Nephritis, Oliguria, Urinary retention

6.2 Postmarketing Experience with LYRICA

The following adverse reactions have been identified during post-approval use of LYRICA. These adverse reactions have not been listed above and data are insufficient to support an estimate of their incidence or to establish causation. The listing is alphabetized: breast enlargement, bullous pemphigoid, gynecomastia.

There are postmarketing reports of life-threatening or fatal respiratory depression in patients taking pregabalin with opioids or other CNS depressants, or in the setting of underlying respiratory impairment.

In addition, there are postmarketing reports of events related to reduced lower gastrointestinal tract function (e.g., intestinal obstruction, paralytic ileus, constipation) when LYRICA was co-administered with medications that have the potential to produce constipation, such as opioid analgesics.

There are postmarketing reports of withdrawal symptoms after discontinuation of pregabalin. Reported adverse reactions include, but are not limited to, seizures, depression, suicidal ideation and behavior, agitation, confusion, disorientation, psychotic symptoms, anxiety, insomnia, nausea, pain, sweating, tremor, headache, dizziness, malaise, and diarrhea.

7 DRUG INTERACTIONS

Since pregabalin is predominantly excreted unchanged in the urine, undergoes negligible metabolism in humans (less than 2% of a dose recovered in urine as metabolites), and does not bind to plasma proteins, its pharmacokinetics are unlikely to be affected by other agents through metabolic interactions or protein binding displacement. In vitro studies showed that pregabalin is unlikely to be involved in significant pharmacokinetic drug interactions [see Clinical Pharmacology (12)].

The interactions of LYRICA CR with co-administration of other drugs have not been systematically evaluated. Co-administration of the prokinetic drug erythromycin with LYRICA CR did not result in any clinically important changes in the pharmacokinetics of LYRICA CR [see Clinical Pharmacology (12)].

Additional studies have been performed with LYRICA. No pharmacokinetic interactions were observed between LYRICA and carbamazepine, gabapentin, lamotrigine, oral contraceptive, phenobarbital, phenytoin, topiramate, and valproic acid. A similar lack of pharmacokinetic interactions would be expected to occur with LYRICA CR.

Pharmacodynamics

Although no pharmacokinetic interactions were seen with LYRICA and ethanol, lorazepam, or oxycodone, additive effects on cognitive and gross motor functioning were seen when LYRICA was co-administered with these drugs. No clinically important effects on respiration were seen in studies of LYRICA.

8 USE IN SPECIFIC POPULATIONS

8.1 Pregnancy

Pregnancy Exposure Registry

There is a pregnancy exposure registry that monitors pregnancy outcomes in women exposed to pregabalin during pregnancy. To provide information regarding the effects of in utero exposure to LYRICA CR, physicians are advised to recommend that pregnant patients taking LYRICA CR enroll in the North American Antiepileptic Drug (NAAED) Pregnancy Registry. This can be done by calling the toll free number 1-888-233-2334, and must be done by patients themselves. Information on the registry can also be found at the website http://www.aedpregnancyregistry.org/.

Risk Summary

Observational studies on the use of Lyrica CR during pregnancy suggest a possible small increase in the rate of overall major birth defects, but there was no consistent or specific pattern of major birth defects identified (see Data). Available postmarketing data on miscarriage and other maternal, fetal, and long term developmental adverse effects were insufficient to identify risk associated with pregabalin.

Postmarketing data suggest that extended gabapentinoid use with opioids close to delivery may increase the risk of neonatal withdrawal versus opioids alone (see Clinical Considerations). There are no comparative epidemiologic studies evaluating this association. Therefore, it is not known whether exposure to pregabalin alone late in pregnancy may cause withdrawal signs and symptoms.

In animal reproduction studies, increased incidences of fetal structural abnormalities and other manifestations of developmental toxicity, including skeletal malformations, retarded ossification, and decreased fetal body weight were observed in the offspring of rats and rabbits given pregabalin orally during organogenesis, at doses that produced plasma pregabalin exposures (AUC) greater than or equal to 18 times human exposure at the maximum recommended dose (MRD) of 660 mg/day (see Data). In an animal development study, lethality, growth retardation, and nervous and reproductive system functional impairment were observed in the offspring of rats given pregabalin during gestation and lactation. The no-effect dose for developmental toxicity was approximately twice the human exposure at MRD.

The estimated background risk of major birth defects and miscarriage for the indicated populations are unknown. All pregnancies have a background risk of birth defect, loss, or other adverse outcomes. In the U.S. general population, the estimated background risk of major birth defects and miscarriage in clinically recognized pregnancies is 2 to 4% and 15 to 20%, respectively.

Clinical Considerations

Fetal/Neonatal Adverse Reactions

Neonatal withdrawal syndrome has been reported in newborns exposed to gabapentinoids in utero for an extended period of time when also exposed to opioids close to delivery. Neonatal withdrawal signs and symptoms reported have included tachypnea, vomiting, diarrhea, hypertonia, irritability, sneezing, poor feeding, hyperactivity, abnormal sleep pattern, and tremor. Reported signs and symptoms that may also be related to withdrawal include tongue thrusting, wandering eye movements while awake, back arching, and continuous extremity movements. Observe neonates exposed to LYRICA CR and opioids for signs and symptoms of neonatal withdrawal and manage accordingly.

Data

Human Data

One database study, which included over 2,700 pregnancies exposed to pregabalin (monotherapy) during the first trimester compared to 3,063,251 pregnancies unexposed to antiepileptics demonstrated prevalence ratios for major malformations overall of 1.14 (CI 95% 0.96-1.35) for pregabalin, 1.29 (CI 95% 1.01-1.65) for lamotrigine, 1.39 (CI 95% 1.07-1.82) for duloxetine, and 1.24 (CI 95% 1.00-1.54) for exposure to either lamotrigine or duloxetine. Important study limitations include uncertainty of whether women who filled a prescription took the medication and inability to adequately control for the underlying disease and other potential confounders.

A published study included results from two separate databases. One database, which included 353 pregnancies exposed to pregabalin (monotherapy) during the first trimester compared to 368,489 pregnancies unexposed to antiepileptics, showed no increase in risk of major birth defects; adjusted relative risk 0.87 (CI 95% 0.53-1.42). The second database, which included 118 pregnancies exposed to pregabalin (monotherapy) during the first trimester compared to 380,347 pregnancies unexposed to antiepileptics, suggested a small increase in risk of major birth defects; adjusted relative risk 1.26 (CI 95% 0.64-2.49). The risk estimates crossed the null, and the study had limitations similar to the prior study.

Other published epidemiologic studies reported inconsistent findings. No specific pattern of birth defects was identified across studies. All of the studies had limitations due to their retrospective design.

Animal Data

When pregnant rats were given pregabalin (500, 1250, or 2500 mg/kg) orally throughout the period of organogenesis, incidences of specific skull alterations attributed to abnormally advanced ossification (premature fusion of the jugal and nasal sutures) were increased at greater than or equal to 1250 mg/kg, and incidences of skeletal variations and retarded ossification were increased at all doses. Fetal body weights were decreased at the highest dose. The low dose in this study was associated with a plasma exposure (AUC) approximately 18 times human exposure at the MRD of 660 mg/day. A no-effect dose for rat embryo-fetal developmental toxicity was not established.

When pregnant rabbits were given pregabalin (250, 500, or 1250 mg/kg) orally throughout the period of organogenesis, decreased fetal body weight and increased incidences of skeletal malformations, visceral variations, and retarded ossification were observed at the highest dose. The no-effect dose for developmental toxicity in rabbits (500 mg/kg) was associated with a plasma exposure approximately 17 times human exposure at the MRD.

In a study in which female rats were dosed with pregabalin (50, 100, 250, 1250, or 2500 mg/kg) throughout gestation and lactation, offspring growth was reduced at greater than or equal to 100 mg/kg and offspring survival was decreased at greater than or equal to 250 mg/kg. The effect on offspring survival was pronounced at doses greater than or equal to 1250 mg/kg, with 100% mortality in high-dose litters. When offspring were tested as adults, neurobehavioral abnormalities (decreased auditory startle responding) were observed at greater than or equal to 250 mg/kg and reproductive impairment (decreased fertility and litter size) was seen at 1250 mg/kg. The no-effect dose for pre- and postnatal developmental toxicity in rats (50 mg/kg) produced a plasma exposure approximately 2 times human exposure at the MRD.

In the prenatal-postnatal study in rats, pregabalin prolonged gestation and induced dystocia at exposures greater than or equal to 50 times the mean human exposure (AUC(0-24) of 123 µg∙hr/mL) at the MRD.

8.2 Lactation

Risk Summary

Small amounts of pregabalin have been detected in the milk of lactating women. A pharmacokinetic study in lactating women detected pregabalin in breast milk at average steady-state concentrations approximately 76% of those in maternal plasma. The estimated average daily infant dose of pregabalin from breast milk (assuming mean milk consumption of 150 mL/kg/day) was 0.31 mg/kg/day, which on a mg/kg basis would be approximately 7% of the maternal dose (see Data). The study did not evaluate the effects of pregabalin on milk production or the effects of pregabalin on the breastfed infant.

Based on animal studies, there is a potential risk of tumorigenicity with pregabalin exposure via breast milk to the breastfed infant [see Nonclinical Toxicology (13.1)]. Available clinical study data in patients greater than 12 years of age do not provide a clear conclusion about the potential risk of tumorigenicity with pregabalin [see Warnings and Precautions (5.9)]. Because of the potential risk of tumorigenicity, breastfeeding is not recommended during treatment with LYRICA CR.

Data

A pharmacokinetic study in ten lactating women, who were at least 12 weeks postpartum, evaluated the concentrations of pregabalin in plasma and breast milk. LYRICA 150 mg oral capsule was given every 12 hours (300 mg daily dose) for a total of 4 doses. Pregabalin was detected in breast milk at average steady-state concentrations approximately 76% of those in maternal plasma. The estimated average daily infant dose of pregabalin from breast milk (assuming mean milk consumption of 150 mL/kg/day) was 0.31 mg/kg/day, which on a mg/kg basis would be approximately 7% of the maternal dose. The study did not evaluate the effects of pregabalin on milk production. Infants did not receive breast milk obtained during the dosing period, therefore, the effects of pregabalin on the breastfed infant were not evaluated.

8.3 Females and Males of Reproductive Potential

Infertility

Males

Effects on Spermatogenesis

In a randomized, double‑blind, placebo‑controlled non‑inferiority study to assess the effect of pregabalin on sperm characteristics, healthy male subjects received pregabalin at a daily dose up to 600 mg (n=111) or placebo (n=109) for 13 weeks (1 complete sperm cycle) followed by a 13‑week washout period (off‑drug). A total of 65 subjects in the pregabalin group (59%) and 62 subjects in the placebo group (57%) were included in the per protocol (PP) population. These subjects took study drug for at least 8 weeks, had appropriate timing of semen collections and did not have any significant protocol violations. Among these subjects, approximately 9% of the pregabalin group (6/65) vs. 3% in the placebo group (2/62) had greater than or equal to 50% reduction in mean sperm concentrations from baseline at Week 26 (the primary endpoint). The difference between pregabalin and placebo was within the pre‑specified non‑inferiority margin of 20%. There were no adverse effects of pregabalin on sperm morphology, sperm motility, serum FSH or serum testosterone levels as compared to placebo. In subjects in the PP population with greater than or equal to 50% reduction in sperm concentration from baseline, sperm concentrations were no longer reduced by greater than or equal to 50% in any affected subject after an additional 3 months off‑drug. In 1 subject, however, subsequent semen analyses demonstrated reductions from baseline of greater than or equal to 50% at 9 and 12 months off‑drug. The clinical relevance of these data is unknown.

In the animal fertility study with pregabalin in male rats, adverse reproductive and developmental effects were observed [see Nonclinical Toxicology (13.1)].

8.4 Pediatric Use

The safety and effectiveness of LYRICA CR in pediatric patients have not been established.

Juvenile Animal Toxicity Data

In studies in which pregabalin (50 to 500 mg/kg) was orally administered to young rats from early in the postnatal period (Postnatal Day 7) through sexual maturity, neurobehavioral abnormalities (deficits in learning and memory, altered locomotor activity, decreased auditory startle responding and habituation) and reproductive impairment (delayed sexual maturation and decreased fertility in males and females) were observed at doses greater than or equal to 50 mg/kg. The neurobehavioral changes of acoustic startle persisted at greater than or equal to 250 mg/kg and locomotor activity and water maze performance at greater than or equal to 500 mg/kg in animals tested after cessation of dosing and, thus, were considered to represent long‑term effects. The low effect dose for developmental neurotoxicity and reproductive impairment in juvenile rats (50 mg/kg) was associated with a plasma pregabalin exposure (AUC) approximately equal to human exposure at the maximum recommended dose of 660 mg/day. A no‑effect dose was not established.

8.5 Geriatric Use

In controlled clinical studies of LYRICA in neuropathic pain associated with diabetic peripheral neuropathy, 246 patients were 65 to 74 years of age, and 73 patients were 75 years of age or older.

In controlled clinical studies of LYRICA in neuropathic pain associated with postherpetic neuralgia, 282 patients were 65 to 74 years of age, and 379 patients were 75 years of age or older.

In the LYRICA CR neuropathic pain associated with postherpetic neuralgia study, 422 patients 65 years of age and older received pregabalin.

No overall differences in safety and effectiveness were observed between these patients and younger patients, and other reported clinical experience has not identified differences in responses between the elderly and younger patients, but greater sensitivity of some older individuals cannot be ruled out.

Pregabalin is known to be substantially excreted by the kidney, and the risk of adverse reactions to this drug may be greater in patients with impaired renal function. Because elderly patients are more likely to have decreased renal function, care should be taken in dose selection, and it may be useful to monitor renal function. See Dosage and Administration (2.5) for recommendations for dosing in patients with renal impairment.

9 DRUG ABUSE AND DEPENDENCE

9.1 Controlled Substance

LYRICA CR contains pregabalin, a Schedule V controlled substance.

9.2 Abuse

In a study of recreational users (N=15) of sedative/hypnotic drugs, including alcohol, LYRICA (450 mg, single dose) received subjective ratings of “good drug effect,” “high” and “liking” to a degree that was similar to diazepam (30 mg, single dose). In controlled clinical studies in over 5500 patients, 4% of LYRICA-treated patients and 1% of placebo-treated patients overall reported euphoria as an adverse reaction, though in some patient populations studied, this reporting rate was higher and ranged from 1 to 12%.

Carefully evaluate all patients treated with LYRICA CR for history of drug abuse and observe them for signs of LYRICA CR misuse or abuse (e.g., development of tolerance, dose escalation, drug-seeking behavior).

9.3 Dependence

In clinical studies, following abrupt or rapid discontinuation of LYRICA CR, some patients reported symptoms including insomnia, nausea, headache, diarrhea, or anxiety [see Warnings and Precautions (5.4)], consistent with physical dependence. In the postmarketing setting, in addition to these reported symptoms, other reported adverse reactions include, but are not limited to, seizures, depression, suicidal ideation and behavior, agitation, confusion, disorientation, psychotic symptoms, pain, sweating, tremor, dizziness, and malaise.

10 OVERDOSAGE

Signs, Symptoms and Laboratory Findings of Acute Overdosage in Humans

In the postmarketing experience, the most commonly reported adverse events observed with pregabalin when taken in overdose include reduced consciousness, depression/anxiety, confusional state, agitation, and restlessness. Seizures and heart block have also been reported. Deaths have been reported in the setting of lone LYRICA overdose and in combination with other CNS depressants.

Treatment or Management of Overdose

There is no specific antidote for overdose with pregabalin. If indicated, elimination of unabsorbed drug may be attempted by emesis or gastric lavage; observe usual precautions to maintain the airway. General supportive care of the patient is indicated including monitoring of vital signs and observation of the clinical status of the patient. Contact a Certified Poison Control Center for up-to-date information on the management of overdose with pregabalin.

Pregabalin can be removed by hemodialysis. Standard hemodialysis procedures result in significant clearance of pregabalin (approximately 50% in 4 hours).

11 DESCRIPTION

LYRICA CR (pregabalin extended-release) tablets are for oral use and contain pregabalin. Pregabalin is described chemically as (S)-3-(aminomethyl)-5-methylhexanoic acid. The molecular formula is C8H17NO2 and the molecular weight is 159.23. The chemical structure of pregabalin is:

Pregabalin is a white to off-white, crystalline solid with a pKa1 of 4.2 and a pKa2 of 10.6. It is freely soluble in water and both basic and acidic aqueous solutions. The log of the partition coefficient (n-octanol/0.05M phosphate buffer) at pH 7.4 is - 1.35.

LYRICA CR extended-release tablets are administered orally and contain 82.5, 165, or 330 mg of pregabalin, along with carbomer, colorants, crospovidone, Kollidon SR (polyvinyl acetate, povidone, sodium lauryl sulphate, and silica), magnesium stearate, polyethylene glycol, polyethylene oxide, polyvinyl alcohol, talc, and titanium dioxide as inactive ingredients.

12 CLINICAL PHARMACOLOGY

12.1 Mechanism of Action

Pregabalin binds with high affinity to the alpha2‑delta site (an auxiliary subunit of voltage‑gated calcium channels) in central nervous system tissues. Although the mechanism of action of pregabalin has not been fully elucidated, results with genetically modified mice and with compounds structurally related to pregabalin (such as gabapentin) suggest that binding to the alpha2‑delta subunit may be involved in pregabalin’s anti‑nociceptive and antiseizure effects in animals. In animal models of nerve damage, pregabalin has been shown to reduce calcium‑dependent release of pro‑nociceptive neurotransmitters in the spinal cord, possibly by disrupting alpha2‑delta-containing calcium channel trafficking and/or reducing calcium currents. Evidence from other animal models of nerve damage and persistent pain suggest the anti‑nociceptive activities of pregabalin may also be mediated through interactions with descending noradrenergic and serotonergic pathways originating from the brainstem that modulate pain transmission in the spinal cord.

While pregabalin is a structural derivative of the inhibitory neurotransmitter gamma-aminobutyric acid (GABA), it does not bind directly to GABAA, GABAB, or benzodiazepine receptors, does not augment GABAA responses in cultured neurons, does not alter rat brain GABA concentration or have acute effects on GABA uptake or degradation. However, in cultured neurons prolonged application of pregabalin increases the density of GABA transporter protein and increases the rate of functional GABA transport. Pregabalin does not block sodium channels, is not active at opiate receptors, and does not alter cyclooxygenase enzyme activity. It is inactive at serotonin and dopamine receptors and does not inhibit dopamine, serotonin, or noradrenaline reuptake.

12.3 Pharmacokinetics

LYRICA CR has linear pharmacokinetics with dose‑proportional increases in maximum plasma concentration (Cmax) and area under the plasma concentration‑time curve (AUC) from 82.5‑660 mg/day. Following repeated administration, steady state is achieved within approximately 48‑72 hours.

LYRICA CR administered once daily following an evening meal has equivalent AUC and lower Cmax relative to a comparative dose of LYRICA administered without food twice daily (Table 5). Variability in Cmax and AUC for LYRICA CR is less than or equal to 25%.

Table 5. Steady-State Pharmacokinetics for LYRICA CR 165 mg Once Daily and LYRICA 75 mg Twice Daily
 | LYRICA CR Once Daily | LYRICA BID
N | 24 | 24
Cmax (µg/mL) | 2.0 (17) | 3.2 (21)
Tmax (h) | 8.0 (5.0 - 12.0) | 0.7 (0.7 - 1.5)
AUC24 (µg•h/mL) | 29.4 (17) | 31.5 (18)
Cmin (µg/mL) | 0.44 (24) | 0.59 (25)
Note: Geometric mean (%CV) for AUC24, Cmax, Cmin; median (range) for Tmax.
Abbreviations: AUC24=area under the curve over 24 hours; BID=every 12 hours; Cmax=peak concentrations; Cmin=minimum concentrations; N=Number of subjects; Tmax=time to peak concentrations.

Absorption

Pregabalin is absorbed from the small intestine and proximal colon. LYRICA CR absorption is linear and dose proportional.

The bioavailability of LYRICA CR is reduced if taken on an empty stomach. The AUC is approximately 30% lower when LYRICA CR is administered fasted relative to following an evening meal.

When LYRICA CR is administered following a 600 to 750 calorie (50% carbohydrates, 20% protein, 30% fat) evening meal, peak plasma concentrations occur within approximately 8 to 10 hours and AUC is approximately 93% to 97% relative to a comparative dose of LYRICA. The rate and extent of LYRICA CR absorption is similar when administered following a 400 to 500 calorie, 30% fat or an 800 to 1000 calorie, 15%, 30%, or 50% fat evening meal.

When LYRICA CR is administered following an 800 to 1000 calorie (50% carbohydrates, 20% protein, 30% fat) morning meal, peak plasma concentrations occur within approximately 12 hours and AUC is 99% relative to a comparative dose of LYRICA. AUC decreases approximately 13% to 25% when LYRICA CR is administered following a 400 to 500 calorie or 600 to 750 calorie (50% carbohydrates, 20% protein, 30% fat) morning meal relative to the 800 to 1000 calorie meal, while Cmax remains the same.

Distribution

Pregabalin does not bind to plasma proteins. The apparent volume of distribution of pregabalin following oral administration is approximately 0.5 L/kg. Pregabalin is a substrate for system L transporter which is responsible for the transport of large amino acids across the blood brain barrier. Although there are no data in humans, pregabalin has been shown to cross the blood brain barrier in mice, rats, and monkeys. In addition, pregabalin has been shown to cross the placenta in rats and is present in the milk of lactating rats.

Elimination

Metabolism

Pregabalin undergoes negligible metabolism in humans. Following a dose of radiolabeled pregabalin, approximately 90% of the administered dose was recovered in the urine as unchanged pregabalin. The N-methylated derivative of pregabalin, the major metabolite of pregabalin found in urine, accounted for 0.9% of the dose. In preclinical studies, pregabalin (S-enantiomer) did not undergo racemization to the R-enantiomer in mice, rats, rabbits, or monkeys.

Excretion

Pregabalin is eliminated from the systemic circulation primarily by renal excretion as unchanged drug with a mean elimination half-life of 6.3 hours in subjects with normal renal function. Mean renal clearance was estimated to be 67.0 to 80.9 mL/min in young healthy subjects. Because pregabalin is not bound to plasma proteins this clearance rate indicates that renal tubular reabsorption is involved. Pregabalin elimination is nearly proportional to CLcr [see Dosage and Administration (2.5)].

Specific Populations

Age: Geriatric Patients

Pregabalin oral clearance tended to decrease with increasing age. This decrease in pregabalin oral clearance is consistent with age-related decreases in CLcr. Reduction of pregabalin dose may be required in patients who have age-related compromised renal function [see Dosage and Administration (2.5)].

Sex

Population pharmacokinetic analyses of the clinical studies showed that the relationship between daily dose and LYRICA CR drug exposure is similar between genders.

Race/Ethnicity

In population pharmacokinetic analyses of the clinical studies of LYRICA and LYRICA CR, the pharmacokinetics of pregabalin were not significantly affected by race (Caucasians, Blacks, and Hispanics).

Renal Impairment

Pregabalin clearance is nearly proportional to CLcr. Dosage reduction in patients with reduced renal function is necessary. Pregabalin is effectively removed from plasma by hemodialysis. Following a 4-hour hemodialysis treatment, plasma pregabalin concentrations are reduced by approximately 50%. For patients on hemodialysis, treatment with LYRICA CR is not recommended [see Dosage and Administration (2.5)].

Drug Interaction Studies

In vitro studies showed that pregabalin is unlikely to be involved in significant pharmacokinetic drug interactions. Pregabalin, at concentrations that were, in general, 10-times those attained in clinical trials, does not inhibit human CYP1A2, CYP2A6, CYP2C9, CYP2C19, CYP2D6, CYP2E1, and CYP3A4 enzyme systems. In vitro drug interaction studies demonstrate that pregabalin does not induce CYP1A2 or CYP3A4 activity. Therefore, an increase in the metabolism of co-administered CYP1A2 substrates (e.g., theophylline, caffeine) or CYP3A4 substrates (e.g., midazolam, testosterone) is not anticipated.

In Vivo Studies

With the exception of erythromycin, the interactions of LYRICA CR with co-administration of other drugs have not been systematically evaluated.

Additional studies have been performed with LYRICA [see Drug Interactions (7)]. No pharmacokinetic interactions were observed between LYRICA and carbamazepine, ethanol, gabapentin, lamotrigine, lorazepam, oral contraceptive, oxycodone, phenobarbital, phenytoin, topiramate, and valproic acid. A similar lack of pharmacokinetic interactions would be expected to occur with LYRICA CR.

The drug interaction studies described in this section were conducted in healthy adults, and across various patient populations.

Erythromycin

Multiple-dose administration of erythromycin (500 mg every 6 hours for 18 hours) in healthy subjects resulted in a 17% decrease in AUC of LYRICA CR (330 mg single dose).

Ethanol

Multiple-dose administration of pregabalin (300 mg twice a day) in healthy subjects had no effect on the rate and extent of ethanol single-dose pharmacokinetics and single-dose administration of ethanol (0.7 g/kg) had no effect on the steady-state pharmacokinetics of pregabalin. Additive effects on cognitive and gross motor functioning were seen when LYRICA was co-administered with ethanol. No clinically important effects on respiration were seen [see Drug Interactions (7)].

Gabapentin

The pharmacokinetic interactions of pregabalin and gabapentin were investigated in 12 healthy subjects following concomitant single‑dose administration of 100‑mg pregabalin and 300‑mg gabapentin and in 18 healthy subjects following concomitant multiple‑dose administration of 200‑mg pregabalin every 8 hours and 400‑mg gabapentin every 8 hours. Gabapentin pharmacokinetics following single‑ and multiple‑dose administration were unaltered by pregabalin co-administration. The extent of pregabalin absorption was unaffected by gabapentin co-administration, although there was a small reduction in rate of absorption.

Lorazepam

Multiple-dose administration of pregabalin (300 mg twice a day) in healthy subjects had no effect on the rate and extent of lorazepam single‑dose pharmacokinetics and single‑dose administration of lorazepam (1 mg) had no effect on the steady‑state pharmacokinetics of pregabalin. Additive effects on cognitive and gross motor functioning were seen when LYRICA was co‑administered with lorazepam. No clinically important effects on respiration were seen [see Drug Interactions (7)].

Oral Contraceptive

Pregabalin co-administration (200 mg 3 times a day) had no effect on the steady‑state pharmacokinetics of norethindrone and ethinyl estradiol (1 mg/35 μg, respectively) in healthy subjects.

Oxycodone

Multiple-dose administration of pregabalin (300 mg twice a day) in healthy subjects had no effect on the rate and extent of oxycodone single‑dose pharmacokinetics. Single‑dose administration of oxycodone (10 mg) had no effect on the steady‑state pharmacokinetics of pregabalin. Additive effects on cognitive and gross motor functioning were seen when LYRICA was co‑administered with oxycodone. No clinically important effects on respiration were seen [see Drug Interactions (7)].

Carbamazepine, Lamotrigine, Phenobarbital, Phenytoin, Topiramate and Valproic Acid

Steady-state trough plasma concentrations of phenytoin, carbamazepine, and carbamazepine 10,11 epoxide, valproic acid, and lamotrigine were not affected by concomitant pregabalin (200 mg 3 times a day) administration.

Population pharmacokinetic analyses in patients treated with pregabalin and various concomitant medications suggest the following:

Therapeutic class | Specific concomitant drug studied
Concomitant drug has no effect on the pharmacokinetics of pregabalin
Hypoglycemics | Glyburide, insulin, metformin
Diuretics | Furosemide
Antiepileptic Drugs | Tiagabine
Concomitant drug has no effect on the pharmacokinetics of pregabalin and pregabalin has no effect on the pharmacokinetics of concomitant drug
Antiepileptic Drugs | Carbamazepine, lamotrigine, phenobarbital, phenytoin, topiramate, valproic acid

13 NONCLINICAL TOXICOLOGY

13.1 Carcinogenesis, Mutagenesis, Impairment of Fertility

Carcinogenesis

A dose‑dependent increase in the incidence of malignant vascular tumors (hemangiosarcomas) was observed in 2 strains of mice (B6C3F1 and CD‑1) given pregabalin (200, 1000, or 5000 mg/kg) in the diet for 2 years. Plasma pregabalin exposure (AUC) in mice receiving the lowest dose that increased hemangiosarcomas was approximately equal to the human exposure at the maximum recommended human dose (MRD) of 660 mg/day. A no‑effect dose for induction of hemangiosarcomas in mice was not established. No evidence of carcinogenicity was seen in 2 studies in Wistar rats following dietary administration of pregabalin for 2 years at doses (50, 150, or 450 mg/kg in males and 100, 300, or 900 mg/kg in females) that were associated with plasma exposures in males and females up to approximately 15 and 26 times, respectively, human exposure at the MRD.

Mutagenesis

Pregabalin was not mutagenic in bacteria or in mammalian cells in vitro, was not clastogenic in mammalian systems in vitro and in vivo, and did not induce unscheduled DNA synthesis in mouse or rat hepatocytes.

Impairment of Fertility

In fertility studies in which male rats were orally administered pregabalin (50 to 2500 mg/kg) prior to and during mating with untreated females, a number of adverse reproductive and developmental effects were observed. These included decreased sperm counts and sperm motility, increased sperm abnormalities, reduced fertility, increased preimplantation embryo loss, decreased litter size, decreased fetal body weights, and an increased incidence of fetal abnormalities. Effects on sperm and fertility parameters were reversible in studies of this duration (3-4 months). The no‑effect dose for male reproductive toxicity in these studies (100 mg/kg) was associated with a plasma pregabalin exposure (AUC) approximately 4 times human exposure at the MRD of 660 mg/day.

In addition, adverse reactions on reproductive organ (testes, epididymides) histopathology were observed in male rats exposed to pregabalin (500 to 1250 mg/kg) in general toxicology studies of 4 weeks or greater duration. The no‑effect dose for male reproductive organ histopathology in rats (250 mg/kg) was associated with a plasma exposure approximately 10 times human exposure at the MRD.

In a fertility study in which female rats were given pregabalin (500, 1250, or 2500 mg/kg) orally prior to and during mating and early gestation, disrupted estrous cyclicity and an increased number of days to mating were seen at all doses, and embryolethality occurred at the highest dose. The low dose in this study produced a plasma exposure approximately 10 times that in humans receiving the MRD. A no‑effect dose for female reproductive toxicity in rats was not established.

13.2 Animal Toxicology and/or Pharmacology

Dermatopathy

Skin lesions ranging from erythema to necrosis were seen in repeated‑dose toxicology studies in both rats and monkeys. The etiology of these skin lesions is unknown. At the MRD of 660 mg/day, there is a 2‑fold safety margin for the dermatological lesions. The more severe dermatopathies involving necrosis were associated with pregabalin exposures (as expressed by plasma AUCs) of approximately 3 to 8 times those achieved in humans given the MRD. No increase in incidence of skin lesions was observed in clinical studies.

Ocular Lesions

Ocular lesions (characterized by retinal atrophy [including loss of photoreceptor cells] and/or corneal inflammation/mineralization) were observed in 2 lifetime carcinogenicity studies in Wistar rats. These findings were observed at plasma pregabalin exposures (AUC) greater than or equal to 2 times those achieved in humans given the maximum recommended dose of 660 mg/day. A no‑effect dose for ocular lesions was not established. Similar lesions were not observed in lifetime carcinogenicity studies in 2 strains of mice or in monkeys treated for 1 year.

14 CLINICAL STUDIES

14.1 Management of Postherpetic Neuralgia (Study PHN CR)

Support for efficacy of LYRICA CR for the management of PHN and diabetic peripheral neuropathy (DPN) was based on the efficacy of LYRICA for these indications along with an adequate and well‑controlled study in adults with PHN. This 19‑week randomized withdrawal study compared daily doses of LYRICA CR 82.5 mg, 165 mg, 247.5 mg, 330 mg, 495 mg, or 660 mg with placebo. Those enrolled were required to have pain present for more than 3 months after healing of the herpes zoster skin rash and a baseline pain score of greater than or equal to 4 on the numeric rating scale (NRS)‑Pain (assessed over a 1 week recall period). The baseline mean pain scores were 6.83 for LYRICA CR‑treated patients vs. 6.85 for placebo‑treated patients. A total of 82.4% of patients completed the single‑blind phase of the study. Patients were considered responders if they had at least a 50% reduction in pain in the single‑blind phase. Those who responded to treatment were then randomized in the double‑blind phase to treatment with either the LYRICA CR dose achieved in the single‑blind phase or placebo. Patients were treated for up to 3 months following randomization. A total of 87.5% of LYRICA CR‑treated patients and 78% of placebo‑treated patients completed the double-blind phase of the study.

LYRICA CR treatment demonstrated statistically significant improvement in the endpoint change in mean pain score from baseline compared to placebo. For a range of levels of improvement in pain intensity from baseline to study endpoint, Figure 1 shows the fraction of patients achieving that degree of improvement. The figure is cumulative, so that patients whose change from baseline is, for example, 50%, are also included at every level of improvement below 50%. Patients who did not complete the study were assigned 0% improvement. In the LYRICA CR group, 79.8% of subjects achieved at least a 30% improvement and 73.6% at least 50% improvement in pain intensity. In the placebo group, 64.9% of subjects achieved at least a 30% improvement and 54.6% at least a 50% improvement in pain intensity.

Figure 1. Percent of Patients Achieving Various Levels of Improvement in Pain Intensity (N=413)

14.2 Management of Fibromyalgia (Study FM CR)

A double-blind, placebo-controlled, randomized withdrawal trial of LYRICA CR in adults with fibromyalgia failed to demonstrate efficacy.

14.3 Adjunctive Therapy for Adult Patients with Partial Onset Seizures

A double-blind, placebo-controlled, randomized trial of LYRICA CR as adjunctive therapy in adults with partial onset seizures failed to demonstrate efficacy.

16 HOW SUPPLIED/STORAGE AND HANDLING

LYRICA CR is supplied in the following strengths and package configurations:

LYRICA CR Tablets
Package Configuration | Tablet Strength (mg) | NDC | Tablet Description
Bottles of 30 tablets | 82.5 mg | NDC 58151-245-93 | Light blue, film-coated, almond-shaped tablet debossed with “VLE” on one side and “PGN 82.5” on the other side
Bottles of 30 tablets | 165 mg | NDC 58151-246-93 | Beige, film-coated, almond-shaped tablet debossed with “VLE” on one side and “PGN 165” on the other side
Bottles of 30 tablets | 330 mg | NDC 58151-247-93 | Rose, film-coated, almond-shaped tablet debossed with “VLE” on one side and “PGN 330” on the other side

Store at 20°C to 25°C (68°F to 77°F), excursions permitted between 15°C and 30°C (between 59°F and 86°F) in the original package. (See USP Controlled Room Temperature)

17 PATIENT COUNSELING INFORMATION

Advise the patient to read the FDA-approved patient labeling (Medication Guide).

Angioedema

Advise patients that LYRICA CR may cause angioedema, with swelling of the face, mouth (lip, gum, tongue) and neck (larynx and pharynx) that can lead to life-threatening respiratory compromise. Instruct patients to discontinue LYRICA CR and immediately seek medical care if they experience these symptoms [see Warnings and Precautions (5.1)].

Hypersensitivity

Advise patients that LYRICA CR has been associated with hypersensitivity reactions such as skin redness, blisters, hives, rash, dyspnea, and wheezing. Instruct patients to discontinue LYRICA CR and immediately seek medical care if they experience these symptoms [see Warnings and Precautions (5.2)].

Suicidal Thinking and Behavior

Counsel patients, their caregivers, and families that AEDs, including pregabalin, the active ingredient in LYRICA CR, may increase the risk of suicidal thoughts and behavior and should be advised of the need to be alert for the emergence or worsening of symptoms of depression, any unusual changes in mood or behavior, or the emergence of suicidal thoughts, behavior, or thoughts about self-harm. Instruct patients, caregivers, and families to report behaviors of concern immediately to a healthcare provider. Also inform patients who plan to or have discontinued LYRICA CR that suicidal thoughts and behavior can appear even after the drug is stopped [see Warnings and Precautions (5.3)].

Respiratory Depression

Inform patients about the risk of respiratory depression. Include information that the risk is greatest for those using concomitant central nervous system (CNS) depressants (such as opioid analgesics) or in those with underlying respiratory impairment. Teach patients how to recognize respiratory depression and advise them to seek medical attention immediately if it occurs [see Warnings and Precautions (5.5)].

Dizziness and Somnolence

Inform patients that LYRICA CR may cause dizziness, somnolence, blurred vision, and other CNS signs and symptoms. Accordingly, advise patients not to drive, operate complex machinery, or engage in other hazardous activities until they have gained sufficient experience on LYRICA CR to gauge whether or not it affects their mental, visual, and/or motor performance adversely [see Warnings and Precautions (5.6)].

CNS Depressants

Inform patients who require concomitant treatment with central nervous system depressants such as opiates or benzodiazepines that they may experience additive CNS side effects, such as respiratory depression, somnolence, and dizziness [see Warnings and Precautions (5.5, 5.6) and Drug Interactions (7)]. Advise patients to avoid consuming alcohol while taking LYRICA CR, as LYRICA CR may potentiate the impairment of motor skills and sedating effects of alcohol [see Drug Interactions (7)].

Abrupt or Rapid Discontinuation

Advise patients to take LYRICA CR as prescribed. Abrupt or rapid discontinuation may result in insomnia, nausea, headache, anxiety, or diarrhea. Advise patients with seizure disorders that abrupt or rapid discontinuation may increase seizure frequency [see Warnings and Precautions (5.4)].

Missed Dose

Instruct patients that if they miss taking their dose of LYRICA CR after an evening meal, then they should take their usual dose of LYRICA CR prior to bedtime following a snack. If they miss taking the dose of LYRICA CR prior to bedtime, then they should take their usual dose of LYRICA CR following a morning meal. If they miss taking the dose of LYRICA CR following the morning meal, then they should take their usual dose of LYRICA CR at the usual time that evening following an evening meal.

Weight Gain and Edema

Inform patients that LYRICA CR may cause edema and weight gain. Advise patients that concomitant treatment with LYRICA CR and a thiazolidinedione antidiabetic agent may lead to an additive effect on edema and weight gain. Advise patients with preexisting cardiac conditions that this may increase the risk of heart failure [see Warnings and Precautions (5.7, 5.8)].

Ophthalmological Effects

Counsel patients that LYRICA CR may cause visual disturbances. Inform patients that if changes in vision occur, they should notify their physician [see Warnings and Precautions (5.10)].

Creatine Kinase Elevations

Instruct patients to promptly report unexplained muscle pain, tenderness, or weakness, particularly if accompanied by malaise or fever [see Warnings and Precautions (5.11)].

Use in Pregnancy

Instruct patients to inform their healthcare provider if they are pregnant or intend to become pregnant during therapy, and to notify their physician if they are breast feeding or intend to breast feed during therapy [see Use in Specific Populations (8.1) and (8.2)].

Encourage patients to enroll in the North American Antiepileptic Drug (NAAED) Pregnancy Registry if they become pregnant. This registry is collecting information about the safety of antiepileptic drugs during pregnancy. To enroll, patients can call the toll-free number 1-888-233-2334 [see Use in Specific Populations (8.1)].

Lactation

Advise nursing mothers that breastfeeding is not recommended during treatment with LYRICA CR [see Use in Specific Populations (8.2)].

Male Fertility

Inform men being treated with LYRICA CR who plan to father a child of the potential risk of male-mediated teratogenicity [see Nonclinical Toxicology (13.1) and Use in Specific Populations (8.3)].

Dermatopathy

Instruct diabetic patients to pay particular attention to skin integrity while being treated with LYRICA CR [see Nonclinical Toxicology (13.2)].

Distributed by:
Viatris Specialty LLC
Morgantown, WV 26505 U.S.A.

© 2025 Viatris Inc.

LYRICA is a registered trademark of Viatris Specialty LLC, a Viatris Company.

The brands listed are trademarks of their respective owners.

UPJ:LYRCCR:R2

MEDICATION GUIDE

LYRICA (LEER-i-kah) CR
(pregabalin)
extended-release tablets, CV

Read this Medication Guide before you start taking LYRICA CR and each time you get a refill. There may be new information. This information does not take the place of talking to your healthcare provider about your medical condition or treatment. If you have any questions about LYRICA CR, ask your healthcare provider or pharmacist.

What is the most important information I should know about LYRICA CR?

LYRICA CR may cause serious side effects including:

- Serious, even life-threatening, allergic reactions
- Suicidal thoughts or actions
- Serious breathing problems

- Swelling of your hands, legs and feet
- Dizziness and sleepiness

These serious side effects are described below:

- Serious, even life-threatening, allergic reactions.
  Stop taking LYRICA CR and call your healthcare provider right away if you have any of these signs of a serious allergic reaction:
  - swelling of your face, mouth, lips, gums, tongue, throat, or neck
  - trouble breathing
  - rash, hives (raised bumps), or blisters
  - skin redness

- Like other antiepileptic drugs, LYRICA CR may cause suicidal thoughts or actions in a very small number of people, about 1 in 500. This can happen while you take LYRICA CR or after stopping. Call a healthcare provider right away if you have any of these symptoms, especially if they are new, worse, or worry you:

- thoughts about suicide or dying
- attempts to commit suicide
- new or worse depression
- new or worse anxiety
- feeling agitated or restless
- panic attacks

- trouble sleeping (insomnia)
- new or worse irritability
- acting aggressive, being angry, or violent
- acting on dangerous impulses
- an extreme increase in activity and talking (mania)
- other unusual changes in behavior or mood

If you have suicidal thoughts or actions, do not stop LYRICA CR without first talking to a healthcare provider.

  - Stopping LYRICA CR suddenly can cause serious problems.
  - Suicidal thoughts or actions can be caused by things other than medicines. If you have suicidal thoughts or actions, your healthcare provider may check for other causes.

How can I watch for early symptoms of suicidal thoughts and actions?

- Pay attention to any changes, especially sudden changes, in mood, behaviors, thoughts, or feelings.
- Keep all follow-up visits with your healthcare provider as scheduled.
- Call your healthcare provider between visits as needed, especially if you are worried about symptoms.

- Serious breathing problems can occur when LYRICA is taken with other medicines that can cause severe sleepiness or decreased awareness, or when it is taken by someone who already has breathing problems. Watch for increased sleepiness or decreased breathing when starting LYRICA or when the dose is increased. Get help right away if breathing problems occur.
- Swelling of your hands, legs and feet. This swelling can be a serious problem for people with heart problems.
- Dizziness and sleepiness. Do not drive a car, work with machines, or do other dangerous activities until you know how LYRICA CR affects you. Ask your healthcare provider about when it will be okay to do these activities.

What is LYRICA CR?

LYRICA CR is a prescription medicine used to treat:

- pain from damaged nerves (neuropathic pain) that happens with diabetes
- pain from damaged nerves (neuropathic pain) that follows healing of shingles

It is not known if LYRICA CR is safe and effective in children.

It is not known if LYRICA CR is effective when used for the treatment of fibromyalgia, or when taken with other seizure medicines for adults with partial onset seizures.

Who should not take LYRICA CR?

Do not take LYRICA CR if you are allergic to pregabalin or any of the ingredients in LYRICA CR.

See “What is the most important information I should know about LYRICA CR?” for the signs of an allergic reaction.

See the end of this leaflet for a complete list of ingredients in LYRICA CR.

What should I tell my healthcare provider before taking LYRICA CR?

Before taking LYRICA CR, tell your healthcare provider about all your medical conditions, including if you:

- have or have had depression, mood problems or suicidal thoughts or behavior
- have breathing problems
- have kidney problems or get kidney dialysis
- have heart problems including heart failure
- have a bleeding problem or a low blood platelet count
- have abused prescription medicines, street drugs, or alcohol in the past
- have ever had swelling of your face, mouth, tongue, lips, gums, neck, or throat (angioedema)
- plan to father a child. Animal studies have shown that pregabalin, the active ingredient in LYRICA CR, made male animals less fertile and caused sperm to change. Also, in animal studies, birth defects were seen in the offspring (babies) of male animals treated with pregabalin. It is not known if these problems can happen in people who take LYRICA CR.
- are pregnant or plan to become pregnant. It is not known if LYRICA CR will harm your unborn baby. You and your healthcare provider will have to decide if you should take LYRICA CR while you are pregnant.
  - If you become pregnant while taking LYRICA CR, talk to your healthcare provider about registering with the North American Antiepileptic Drug Pregnancy Registry. You can enroll in this registry by calling 1-888-233-2334. The purpose of this registry is to collect information about the safety of antiepileptic drugs, including pregabalin, the active ingredient in LYRICA CR. Information about the registry can be found at the website, http://www.aedpregnancyregistry.org/.
- are breastfeeding or plan to breastfeed. LYRICA CR passes into your breast milk. It is not known if LYRICA CR can harm your baby. Talk to your healthcare provider about the best way to feed your baby if you take LYRICA CR. Breastfeeding is not recommended while taking LYRICA CR.

Tell your healthcare provider about all the medicines you take, including prescription and over-the-counter medicines, vitamins or herbal supplements. LYRICA CR and other medicines may affect each other causing side effects. Especially tell your healthcare provider if you take:

- angiotensin converting enzyme (ACE) inhibitors, which are used to treat many conditions, including high blood pressure. You may have a higher chance for swelling and hives if these medicines are taken with LYRICA CR. See “What is the most important information I should know about LYRICA CR?”
- Avandia® (rosiglitazone), Avandamet® (contains rosiglitazone and metformin), or Actos® (pioglitazone) for diabetes. You may have a higher chance of weight gain or swelling of your hands or feet if these medicines are taken with LYRICA CR. See “What are the possible side effects of LYRICA CR.”
- any opioid pain medicine (such as oxycodone), or medicines for anxiety (such as lorazepam) or insomnia (such as zolpidem). You may have a higher chance for dizziness, sleepiness or serious breathing problems if these medicines are taken with LYRICA CR.
- any medicines that make you sleepy

Know the medicines you take. Keep a list of them with you to show your healthcare provider and pharmacist each time you get a new medicine. Do not start a new medicine without talking with your healthcare provider.

How should I take LYRICA CR?

- Take LYRICA CR exactly as prescribed. Your healthcare provider will tell you how much LYRICA CR to take and when to take it.
- Take LYRICA CR at the same time each day.
- LYRICA CR must be taken after your evening meal. Swallow the tablet whole and do not split, crush or chew the tablet.
- Your healthcare provider may change your dose. Do not change your dose without talking to your healthcare provider.
- Do not stop taking LYRICA CR without talking to your healthcare provider. If you stop taking LYRICA CR suddenly you may have headaches, nausea, diarrhea, trouble sleeping, or you may feel anxious. If you have epilepsy, are taking LYRICA CR for pain, and stop taking LYRICA CR suddenly, you may have seizures more often. Talk with your healthcare provider about how to stop LYRICA CR slowly.
- If you miss a dose after your evening meal, take it prior to bedtime following a snack. If you miss the dose prior to bedtime, then take it following your morning meal. If you do not take the dose the following morning, then take the next dose at your regular time after your evening meal. Do not take 2 doses at the same time.
- If you take too much LYRICA CR, call your healthcare provider or poison control center, or go to the nearest emergency room right away.

What should I avoid while taking LYRICA CR?

- Do not drive a car, work with machines, or do other dangerous activities until you know how LYRICA CR affects you.
- Do not drink alcohol while taking LYRICA CR. LYRICA CR and alcohol can affect each other and increase side effects such as sleepiness and dizziness.

What are the possible side effects of LYRICA CR?

LYRICA CR may cause serious side effects, including:

- muscle problems, muscle pain, soreness, or weakness. If you have these symptoms, especially if you feel sick and have a fever, tell your healthcare provider right away.
- problems with your eyesight, including blurry vision. Call your healthcare provider if you have any changes in your eyesight.
- weight gain. If you have diabetes, weight gain may affect the management of your diabetes. Weight gain can also be a serious problem for people with heart problems.
- Feeling “high”

The most common side effects of LYRICA CR are:

- dizziness
- blurry vision
- weight gain
- sleepiness
- fatigue (tiredness)

- swelling of hands and feet
- dry mouth
- nausea

LYRICA CR caused skin sores in animal studies. Skin sores did not happen in studies in people. If you have diabetes, you should pay attention to your skin while taking LYRICA CR and tell your healthcare provider about any sores or skin problems.

Tell your healthcare provider about any side effect that bothers you or that does not go away.

These are not all the possible side effects of LYRICA CR. For more information, ask your healthcare provider or pharmacist.

Call your doctor for medical advice about side effects. You may report side effects to FDA at 1-800-FDA-1088.

How should I store LYRICA CR?

- Store LYRICA CR at room temperature between 68°F to 77°F (20°C to 25°C) in its original package.
- Safely throw away any LYRICA CR that is out of date or no longer needed.

Keep LYRICA CR and all medicines out of the reach of children.

General information about the safe and effective use of LYRICA CR.

Medicines are sometimes prescribed for purposes other than those listed in a Medication Guide. Do not use LYRICA CR for a condition for which it was not prescribed. Do not give LYRICA CR to other people, even if they have the same symptoms you have. It may harm them. You can ask your pharmacist or healthcare provider for information about LYRICA CR that is written for health professionals.

You can also call Viatris at 1-877-446-3679 (1-877-4-INFO-RX).

What are the ingredients in LYRICA CR?

Active ingredient: pregabalin

Inactive ingredients: carbomer, colorants, crospovidone, Kollidon SR (polyvinyl acetate, povidone, sodium lauryl sulphate, and silica), magnesium stearate, polyethylene glycol, polyethylene oxide, polyvinyl alcohol, talc, and titanium dioxide.

Distributed by:
Viatris Specialty LLC
Morgantown, WV 26505 U.S.A.

© 2025 Viatris Inc.

LYRICA is a registered trademark of Viatris Specialty LLC, a Viatris Company.

The brands listed are trademarks of their respective owners.

UPJ:MG:LYRCCR:R2

This Medication Guide has been approved by the U.S. Food and Drug Administration. Revised: 04/2025

PRINCIPAL DISPLAY PANEL – 82.5 mg

NDC 58151-245-93

Lyrica® CR CV
(pregabalin)
extended release tablets
82.5 mg

ALWAYS DISPENSE WITH
MEDICATION GUIDE

30 Tablets Rx only

Store at 20°C to 25°C (68°F to 77°F);
excursions permitted between 15°C
and 30°C (between 59°F and 86°F)
in the original package.
[See USP Controlled Room Temperature]

Dispense in tight (USP), child-resistant
containers.

DOSAGE AND USE
See accompanying prescribing information.

Each tablet contains 82.5 mg pregabalin.

Distributed by:
Viatris Specialty LLC
Morgantown, WV 26505 U.S.A.
© 2024 Viatris Inc.

Made in Germany

RUPJ245H

PRINCIPAL DISPLAY PANEL – 165 mg

NDC 58151-246-93

Lyrica® CR CV
(pregabalin)
extended release tablets
165 mg

ALWAYS DISPENSE WITH
MEDICATION GUIDE

30 Tablets Rx only

Store at 20°C to 25°C (68°F to 77°F);
excursions permitted between 15°C
and 30°C (between 59°F and 86°F)
in the original package.
[See USP Controlled Room Temperature]

Dispense in tight (USP), child-resistant
containers.

DOSAGE AND USE
See accompanying prescribing information.

Each tablet contains 165 mg pregabalin.

Distributed by:
Viatris Specialty LLC
Morgantown, WV 26505 U.S.A.
© 2024 Viatris Inc.

Made in Germany

RUPJ246H

PRINCIPAL DISPLAY PANEL – 330 mg

NDC 58151-247-93

Lyrica® CR CV
(pregabalin)
extended release tablets
330 mg

ALWAYS DISPENSE WITH
MEDICATION GUIDE

30 Tablets Rx only

Store at 20°C to 25°C (68°F to 77°F);
excursions permitted between 15°C
and 30°C (between 59°F and 86°F)
in the original package.
[See USP Controlled Room Temperature]

Dispense in tight (USP), child-resistant
containers.

DOSAGE AND USE
See accompanying prescribing information.

Each tablet contains 330 mg pregabalin.

Distributed by:
Viatris Specialty LLC
Morgantown, WV 26505 U.S.A.
© 2024 Viatris Inc.

Made in Germany

RUPJ247H